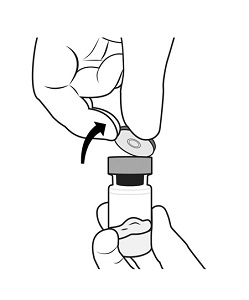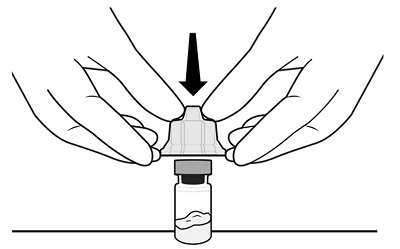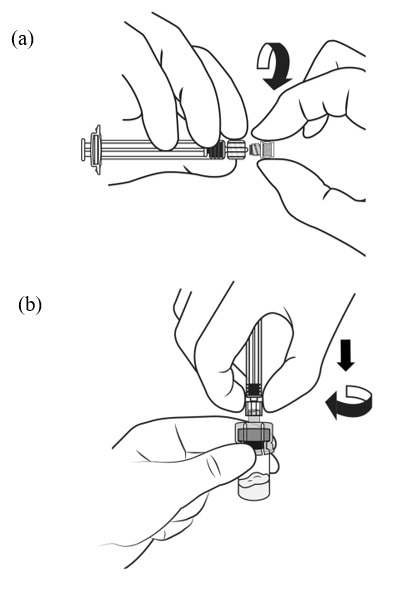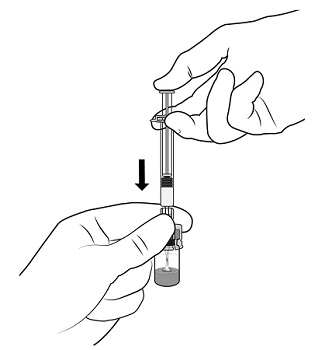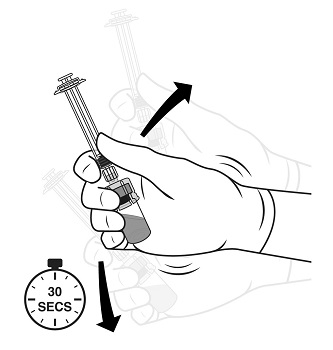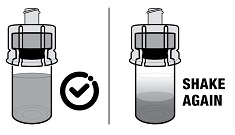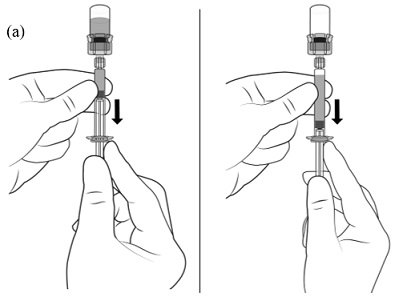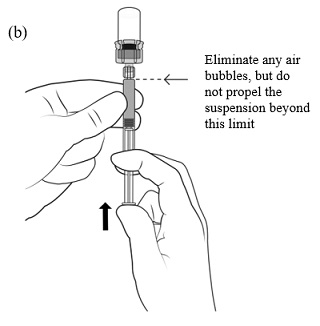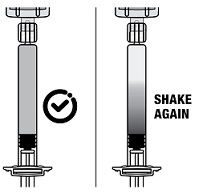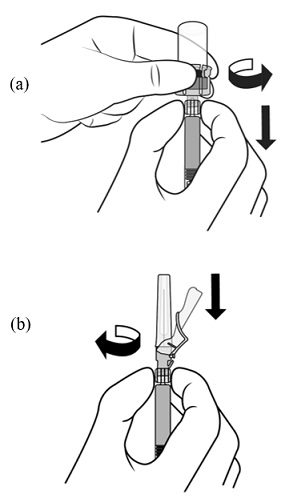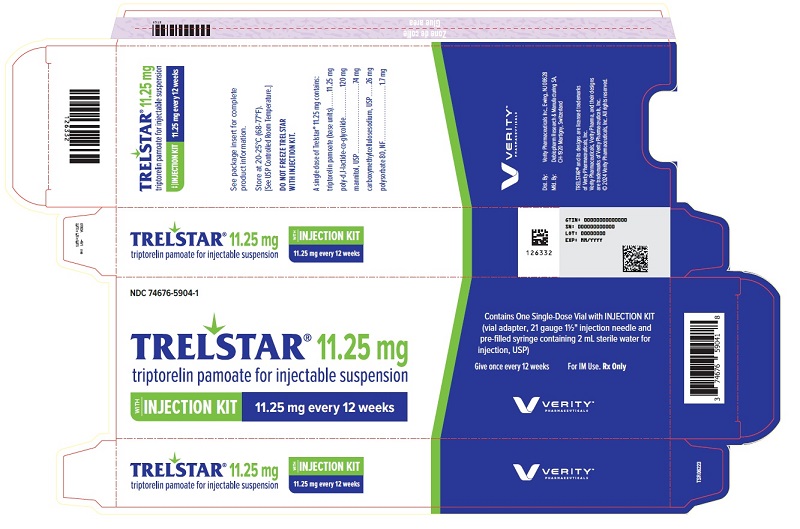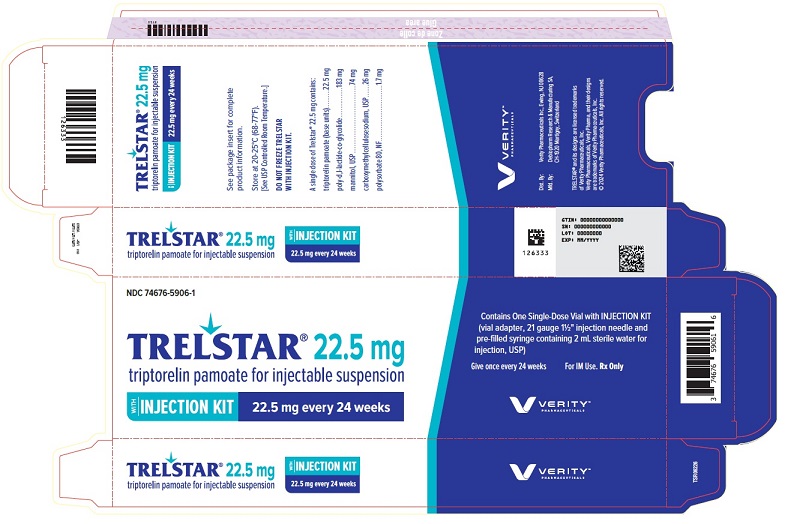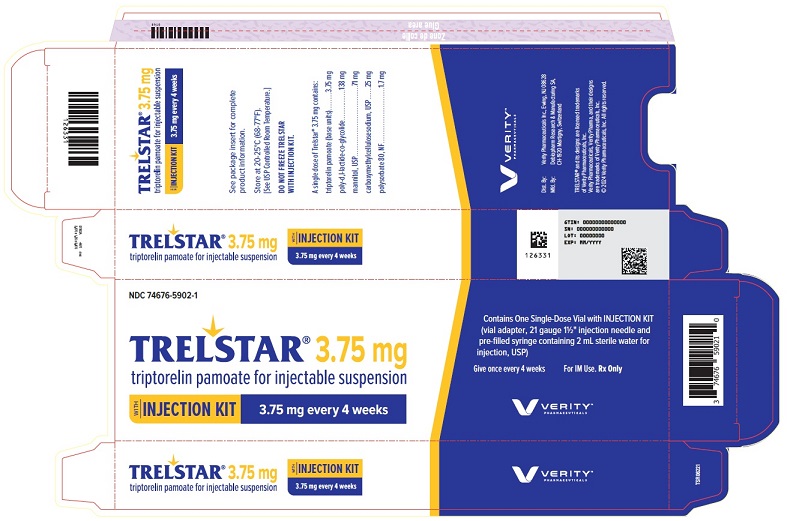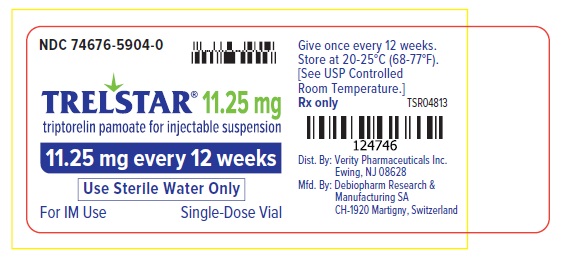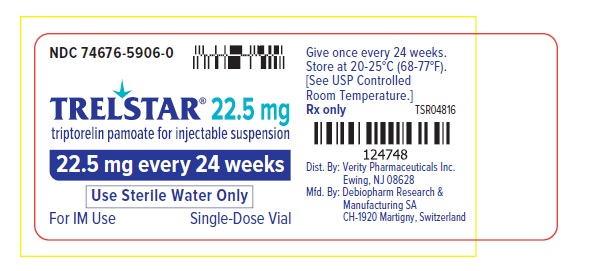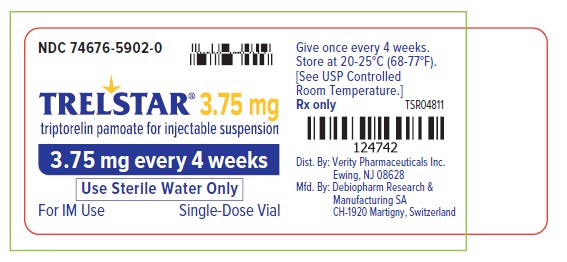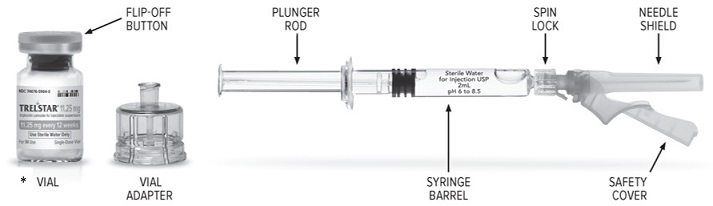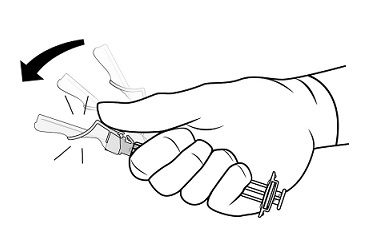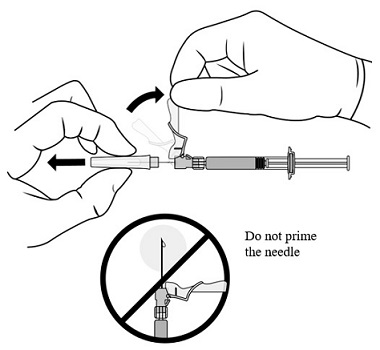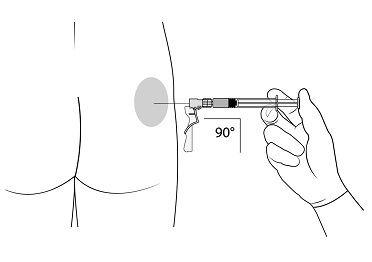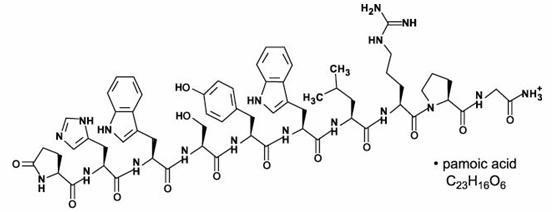 DRUG LABEL: Trelstar
NDC: 74676-5902 | Form: KIT | Route: INTRAMUSCULAR
Manufacturer: Verity Pharmaceuticals Inc.
Category: prescription | Type: HUMAN PRESCRIPTION DRUG LABEL
Date: 20250923

ACTIVE INGREDIENTS: TRIPTORELIN PAMOATE 3.75 mg/2 mL
INACTIVE INGREDIENTS: MANNITOL; CARBOXYMETHYLCELLULOSE SODIUM; POLYSORBATE 80; WATER

HIGHLIGHTS OF PRESCRIBING INFORMATION

These highlights do not include all the information needed to use TRELSTAR safely and effectively. See full prescribing information for TRELSTAR.
TRELSTAR® (triptorelin pamoate for injectable suspension), for intramuscular use
Initial U.S. Approval: 2000

RECENT MAJOR CHANGES

Warnings and Precautions (5.6) | 09/2025

1 INDICATIONS AND USAGE

TRELSTAR is a gonadotropin releasing hormone (GnRH) agonist indicated for the treatment of advanced prostate cancer. (1)

2 DOSAGE AND ADMINISTRATION

TRELSTAR is administered as a single intramuscular injection in either buttock. Due to different release characteristics, the dosage strengths are not additive and must be selected based upon the desired dosing schedule. (2.1)

- 3.75 mg every 4 weeks. (2.1)
- 11.25 mg every 12 weeks. (2.1)
- 22.5 mg every 24 weeks. (2.1)

3 DOSAGE FORMS AND STRENGTHS

For injectable suspension: 3.75 mg, 11.25 mg, 22.5 mg. (3)

4 CONTRAINDICATIONS

- Known hypersensitivity to triptorelin or any other component of the product, or other GnRH agonists or GnRH. (4)

5 WARNINGS AND PRECAUTIONS

- Hypersensitivity: Anaphylactic shock, hypersensitivity, and angioedema have been reported. In the event of a reaction, discontinue TRELSTAR and initiate appropriate medical management. (5.1)
- Tumor Flare: Transient increase in serum testosterone levels can occur within the first few weeks of treatment. This may worsen prostate cancer and result in spinal cord compression and urinary tract obstruction. Monitor patients at risk and manage as appropriate. (5.2)
- Metabolic Syndrome: The use of GnRH agonists may lead to an increased risk of metabolic changes such as hyperglycemia, diabetes, hyperlipidemia, and non-alcoholic fatty liver disease. Monitor for signs and symptoms of metabolic syndrome including lipids, blood glucose level and/or HbA1c and manage according to institutional guidelines. (5.3)
- Cardiovascular Diseases: Increased risk of myocardial infarction, sudden cardiac death and stroke has been reported in men. Monitor for cardiovascular disease and manage according toto institutional guidelines. (5.4)
- Convulsions: Convulsions have occurred in patients treated with GnRH analogs (including TRELSTAR) with or without a history of predisposing factors. Manage patients who experience convulsions according to institutional guidelines. (5.5)
- Severe Cutaneous Adverse Reactions (SCARs): SCARs have been reported in patients receiving GnRH agonists, including triptorelin products. Interrupt TRELSTAR if signs or symptoms of SCARs develop. Permanently discontinue TRELSTAR if a SCAR is confirmed. (5.6)
- Effect on QT/QTc Interval: Androgen deprivation therapy may prolong the QT interval. Consider risks and benefits. (5.7)
- Embryo-Fetal Toxicity: TRELSTAR may cause fetal harm. (5.10, 8.1)

6 ADVERSE REACTIONS

- 3.75 mg: The most common adverse reactions (≥ 5%) during TRELSTAR 3.75 mg therapy included hot flushes, skeletal pain, impotence, and headache. (6.1)
- 11.25 mg: The most common adverse reactions (≥ 5%) during TRELSTAR 11.25 mg therapy included hot flushes, skeletal pain, headache, edema in legs, and leg pain. (6.1)
- 22.5 mg: The most common adverse reactions (≥ 5%) during TRELSTAR 22.5 mg therapy included hot flushes, erectile dysfunction, and testicular atrophy. (6.1)

To report SUSPECTED ADVERSE REACTIONS, contact Verity Pharma at 1-844-837-4891 or FDA at 1-800-FDA-1088 or www.fda.gov/medwatch.

8 USE IN SPECIFIC POPULATIONS

- Females and males of reproductive potential: TRELSTAR may impair fertility. (8.3)

FULL PRESCRIBING INFORMATION

1 INDICATIONS AND USAGE

TRELSTAR is indicated for the treatment of advanced prostate cancer [see Clinical Studies (14)].

2 DOSAGE AND ADMINISTRATION

2.1 Dosing Information

TRELSTAR must be administered under the supervision of a physician.

TRELSTAR is administered by a single intramuscular injection in either buttock. Dosing schedule depends on the product strength selected (Table 1). The lyophilized microgranules are to be reconstituted in sterile water. No other diluent should be used.

Table 1. TRELSTAR Recommended Dosing
Dosage | 3.75 mg | 11.25 mg | 22.5 mg
Recommended dose | 1 injection every 4 weeks | 1 injection every 12 weeks | 1 injection every 24 weeks

Due to different release characteristics, the dosage strengths are not additive and must be selected based upon the desired dosing schedule.

The suspension should be administered within 2 minutes after reconstitution.

As with other drugs administered by intramuscular injection, the injection site should be alternated periodically.

Parenteral drug products should be inspected visually for particulate matter and discoloration prior to administration, whenever solution and container permit.

2.2 Reconstitution Instructions for TRELSTAR

Important: Please read the instructions completely and prepare the patient before you begin the injection kit activation and drug administration procedure.

*The strength indicated on the vial in the figure above is for representative purposes only. All three strengths of the Trelstar vial have their individual strengths indicated on the label. Users will see either 3.75 mg, 11.25 mg or 22.5 mg, with the corresponding duration of treatment (4, 12 or 24 weeks respectively).

Preparation and Activation

Check that you are using the prescribed strength/dose (3.75 mg, 11.25 mg, or 22.5 mg) and that the expiry date has not passed, before preparation and activation.

Wash your hands with soap and hot water and put on gloves immediately prior to preparing the injection. Place the sealed tray on a clean, flat surface that is covered with a sterile pad or cloth. Peel the cover away from the tray and remove the injection kit components and TRELSTAR vial.

General Instructions and Recommendations

- The product is a suspension of microgranules that can settle in the diluent. The final product to be administered is a suspension of microgranules with a milky, homogeneous appearance. If the product settles in the vial, shake it again to resuspend the microgranules.
- If the microgranules settle in the syringe, this will block the needle during administration. It is very important to inject the product within 2 minutes following reconstitution in the vial. If the product settles in the syringe, draw some air back into the syringe, shake it again, and expel the air (without priming the needle) before administering it.

STEP 1 – PREPARE VIAL

Remove the flip-off button cap from the vial, revealing the rubber stopper.
Place the vial in a standing upright position on the prepared surface.
Disinfect the rubber stopper with the alcohol wipe. Discard the alcohol wipe and allow the stopper to dry.

STEP 2 – APPLY VIAL ADAPTER

Peel the cover away from the blister pack containing the vial adapter. Do not remove the vial adapter from the blister pack.
On a level surface, place the blister pack containing the vial adapter firmly on the vial top. Ensure the spike is centered and vertical when piercing the vial. Push down gently until you feel it snap into place.
Remove the blister pack from the vial adapter.

STEP 3 – PREPARE SYRINGE AND CONNECT TO VIAL ADAPTER

(a) Grasp the plastic ‘spin lock’ collar on the syringe barrel with index finger and thumb. Unscrew and discard the gray rubber cap from the syringe barrel.

(b) Maintaining your grip on the spin lock, attach the syringe to the vial adapter by screwing the spin lock clockwise onto the vial adapter luer lock. Gently twist the spin lock until it stops turning to ensure a tight connection.
Note: Overtightening can result in a poor connection and leakage.

STEP 4 – TRANSFER DILUENT TO VIAL

Holding the vial and adapter with one hand, slowly push the plunger rod with the other hand and transfer all of the diluent into the vial.

STEP 5 – MIX TRELSTAR SUSPENSION

Gripping the vial and vial adapter firmly, shake vigorously for 30 seconds to mix the contents thoroughly. This will ensure complete mixing of TRELSTAR and the sterile water diluent.

Check the appearance of the suspension through the bottom of the vial. The suspension should appear homogeneous and milky. In order to avoid separation of the suspension, proceed to the next steps without delay. The product must be injected within less than 2 minutes from reconstitution.

Note: If there is sedimentation in the vial, shake again.

STEP 6 – LOAD THE SYRINGE WITH TRELSTAR

(a) Immediately invert the system so that the vial is at the top and the syringe is at the bottom. Pull back the plunger rod slowly to draw the reconstituted TRELSTAR into the syringe while maintaining pressure on the plunger rod to ensure it does not pull back too far.

(b) Remove air bubbles by expelling air into the vial but do not propel the suspension beyond the luer lock.

Note: If the product settles in the syringe, draw some air back into the syringe, shake it again, and expel the air (without priming the needle) before administering it.

STEP 7 – DISCONNECT VIAL ADAPTER AND CONNECT NEEDLE

(a) Hold the barrel and spin lock firmly.
Hold the syringe barrel and spin lock with one hand and with the other hand turn the adapter counter-clockwise to disconnect the vial adapter and vial from the syringe.
(b) Holding the syringe by the spin lock, attach the injection needle

STEP 8 – PREPARE FOR INJECTION

Make sure that the patient is ready for the administration.
Lift up the safety cover and remove the clear plastic needle shield by pulling it from the assembly. The safety cover should be perpendicular to the needle, with the needle facing away from you. Do not prime the needle.
The syringe containing the TRELSTAR suspension is now ready for administration. The suspension should be administered immediately (less than 2 minutes) after reconstitution to avoid excessive thickening of the suspension.

STEP 9 – ADMINISTRATION
Administer the injection by inserting the needle at a 90-degree angle into the large gluteal muscle. Ensure that the full amount of the product is injected within 10 seconds without interruption.
Injection sites should be alternated.

STEP 10 – SAFETY LOCK AFTER INJECTION

After administering the injection, immediately activate the safety mechanism by centering your thumb or forefinger on the textured finger pad area of the safety cover and pushing it forward over the needle until you hear or feel it lock in place. Use the one-handed technique and activate the mechanism away from yourself and others. Immediately discard the syringe into a sharps container after a single use.

3 DOSAGE FORMS AND STRENGTHS

For injectable suspension: 3.75 mg, 11.25 mg, 22.5 mg of slightly yellow lyophilized microgranules in a single-dose vial for reconstitution with an injection kit containing one syringe filled with sterile water for injection, a vial adapter to help with reconstitution, and one needle (see figure in section 2.2).

4 CONTRAINDICATIONS

4.1 Hypersensitivity

TRELSTAR is contraindicated in individuals with a known hypersensitivity to triptorelin or any other component of the product, or other GnRH agonists or GnRH [see Warnings and Precautions (5.1)].

5 WARNINGS AND PRECAUTIONS

5.1 Hypersensitivity Reactions

Anaphylactic shock, hypersensitivity, and angioedema related to TRELSTAR administration have been reported. In the event of a hypersensitivity reaction, discontinue TRELSTAR immediately and administer the appropriate supportive and symptomatic care.

5.2 Tumor Flare

Initially, triptorelin (TRELSTAR), like other GnRH agonists, causes a transient increase in serum testosterone levels [see Clinical Pharmacology (12.2) ]. As a result, worsening signs and symptoms of prostate cancer during the first weeks of treatment have been reported with GnRH agonists. Patients may experience worsening of symptoms or onset of new symptoms, including bone pain, neuropathy, hematuria, or urethral or bladder outlet obstruction.

Closely monitor patients with metastatic vertebral lesions and/or with urinary tract obstruction during the first few weeks of therapy.

5.3 Metabolic Syndrome

The use of GnRH agonists (including TRELSTAR) may lead to metabolic changes such as hyperglycemia, diabetes mellitus, and hyperlipidemia. Non-alcoholic fatty liver disease, including cirrhosis, occurred in the post-marketing setting. Hyperglycemia may represent new-onset of diabetes mellitus or worsening of glycemic control in patients with pre-existing diabetes. Monitor for changes in serum lipids, blood glucose and/or glycosylated hemoglobin (HbA1c) periodically in patients receiving TRELSTAR and manage according to institutional guidelines.

5.4 Cardiovascular Diseases

Increased risk of developing myocardial infarction, sudden cardiac death and stroke has been reported in association with the use of GnRH agonists (including TRELSTAR) in men. The risk appears low based on the reported odds ratios and should be evaluated carefully along with cardiovascular risk factors when determining a treatment for patients with prostate cancer. Monitor patients receiving TRELSTAR for symptoms and signs suggestive of development of cardiovascular disease and manage according to current institutional guidelines.

5.5 Convulsions

Convulsions have occurred in patients treated with GnRH analog (including TRELSTAR). These events included patients with risk factors for seizures such as a history of epilepsy, intracranial tumors or co-medication with other drugs known to present a risk of seizure reactions. Convulsions have also been reported in patients in the absence of known risk factors. Manage patients receiving TRELSTAR who experience convulsion according to institutional guidelines.

5.6 Severe Cutaneous Adverse Reactions

TRELSTAR can cause severe cutaneous adverse reactions (SCARs), including Stevens-Johnson syndrome/toxic epidermal necrolysis (SJS/TEN), drug reaction with eosinophilia and systemic symptoms (DRESS), and acute generalized exanthematous pustulosis (AGEP). SCARs, including SJS/TEN, DRESS, and AGEP, occurred in patients receiving TRELSTAR or other GnRH agonists; including cases with visceral involvement and/or requiring skin grafts [see Adverse Reactions (6.2)].

Monitor patients for the development of SCARs.

If a SCAR is suspected, interrupt TRELSTAR until the etiology of the reaction has been determined. Consultation with a dermatologist is recommended. If a SCAR is confirmed, or for other grade 4 skin reactions, permanently discontinue TRELSTAR.

5.7 Effect on QT/QTc Interval

Androgen deprivation therapy with TRELSTAR may prolong the QT/QTc interval. Providers should consider whether the benefits of androgen deprivation therapy outweigh the potential risks in patients with congenital long QT syndrome, congestive heart failure, frequent electrolyte abnormalities, and in patients taking drugs known to prolong the QT interval. Electrolyte abnormalities should be corrected. Consider periodic monitoring of electrocardiograms and electrolytes.

5.8 Laboratory Tests

Monitor serum levels of testosterone following injection of TRELSTAR. In the majority of patients, testosterone levels increased above baseline, and then declined thereafter to castrate levels (< 50 ng/dL) within four weeks [see Clinical Studies (14) and Adverse Reactions (6)].

5.9 Laboratory Test Interactions

Chronic or continuous administration of TRELSTAR in therapeutic doses results in suppression of pituitary-gonadal axis. Diagnostic tests of the pituitary-gonadal function conducted during treatment and after cessation of therapy may therefore be misleading.

5.10 Embryo-Fetal Toxicity

Based on findings from animal studies and mechanism of action, TRELSTAR can cause fetal harm when administered to a pregnant woman [Clinical Pharmacology (12.1)]. In animal developmental and reproductive toxicology studies, daily administration of triptorelin to pregnant rats during the period of organogenesis caused maternal toxicity and embryo-fetal toxicities, including loss of pregnancy, at doses as low as 0.2, 0.8, and 8 times the estimated human daily dose based on body surface area. Advise pregnant patients and females of reproductive potential of the potential risk to the fetus [see Use in Specific Populations (8.1)].

6 ADVERSE REACTIONS

The following is discussed in more detail in other sections of the labeling:

- Hypersensitivity Reactions [see Warnings and Precautions (5.1)]
- Tumor Flare [see Warnings and Precautions (5.2)].
- Metabolic Syndrome [see Warnings and Precautions (5.3)]
- Cardiovascular Diseases [see Warnings and Precautions (5.4)].
- Convulsions [see Warnings and Precautions (5.5)].
- Severe Cutaneous Adverse Reactions [see Warnings and Precautions (5.6)].
- Effect of QT/QTc Interval [see Warnings and Precautions (5.7)].

6.1 Clinical Trials Experience

Because clinical trials are conducted under widely varying conditions, adverse reaction rates observed in the clinical trials of a drug cannot be directly compared with rates in the clinical trials of another drug and may not reflect the rates observed in practice.

The safety of the three TRELSTAR formulations was evaluated in clinical trials involving patients with advanced prostate cancer. Mean testosterone levels increased above baseline during the first week following the initial injection, declining thereafter to baseline levels or below by the end of the second week of treatment. The transient increase in testosterone levels may be associated with temporary worsening of disease signs and symptoms, including bone pain, neuropathy, hematuria, and urethral or bladder outlet obstruction. Spinal cord compression with weakness or paralysis of the lower extremities have occurred [see Warnings and Precautions (5.2)].

Adverse reactions reported for each of the three TRELSTAR formulations in the clinical trials, are presented in Table 2, Table 3, and Table 4. The majority of adverse reactions related to TRELSTAR are a result of its pharmacological action, i.e., the induced variation in serum testosterone levels, either an increase in testosterone at the initiation of treatment, or a decrease in testosterone once castration is achieved. Local reactions at the injection site or allergic reactions may occur.

The following adverse reactions were reported to have a possible or probable relationship to therapy as described by the treating physician in at least 1% of patients receiving TRELSTAR 3.75 mg.

Table 2. TRELSTAR 3.75 mg: Treatment-Related Adverse Reactions Reported by 1% or More of Patients During Treatment
Adverse Reactions* | TRELSTAR 3.75 mg N = 140
 | N | %
Application Site Disorders
Injection site pain | 5 | 3.6
Body as a Whole
Hot flush | 82 | 58.6
Pain | 3 | 2.1
Leg pain | 3 | 2.1
Fatigue | 3 | 2.1
Cardiovascular Disorders
Hypertension | 5 | 3.6
Central and Peripheral Nervous System Disorders
Headache | 7 | 5.0
Dizziness | 2 | 1.4
Gastrointestinal Disorders
Diarrhea | 2 | 1.4
Vomiting | 3 | 2.1
Musculoskeletal System Disorders
Skeletal pain | 17 | 12.1
Psychiatric Disorders
Insomnia | 3 | 2.1
Impotence | 10 | 7.1
Emotional lability | 2 | 1.4
Red Blood Cell Disorders
Anemia | 2 | 1.4
Skin and Appendages Disorders
Pruritus | 2 | 1.4
Urinary System Disorders
Urinary tract infection | 2 | 1.4
Urinary retention | 2 | 1.4

* Adverse reactions for TRELSTAR 3.75 mg are coded using the WHO Adverse Reactions Terminology (WHOART)

The following adverse reactions were reported to have a possible or probable relationship to therapy as described by the treating physician in at least 1% of patients receiving TRELSTAR 11.25 mg.

Table 3. TRELSTAR 11.25 mg: Treatment-Related Adverse Reactions Reported by 1% or More of Patients During Treatment
Adverse Reactions* | TRELSTAR 11.25 mg N = 174
 | N | %
Application Site
Injection site pain | 7 | 4.0
Body as a Whole
Hot flush | 127 | 73.0
Leg pain | 9 | 5.2
Pain | 6 | 3.4
Back pain | 5 | 2.9
Fatigue | 4 | 2.3
Chest pain | 3 | 1.7
Asthenia | 2 | 1.1
Peripheral edema | 2 | 1.1
Cardiovascular Disorders
Hypertension | 7 | 4.0
Dependent edema | 4 | 2.3
Central and Peripheral Nervous System Disorders
Headache | 12 | 6.9
Dizziness | 5 | 2.9
Leg cramps | 3 | 1.7
Endocrine
Breast pain | 4 | 2.3
Gynecomastia | 3 | 1.7
Gastrointestinal Disorders
Nausea | 5 | 2.9
Constipation | 3 | 1.7
Dyspepsia | 3 | 1.7
Diarrhea | 2 | 1.1
Abdominal pain | 2 | 1.1
Liver and Biliary System
Abnormal hepatic function | 2 | 1.1
Metabolic and Nutritional Disorders
Edema in legs | 11 | 6.3
Increased alkaline phosphatase | 3 | 1.7
Musculoskeletal System Disorders
Skeletal pain | 23 | 13.2
Arthralgia | 4 | 2.3
Myalgia | 2 | 1.1
Psychiatric Disorders
Decreased libido | 4 | 2.3
Impotence | 4 | 2.3
Insomnia | 3 | 1.7
Anorexia | 3 | 1.7
Respiratory System Disorders
Coughing | 3 | 1.7
Dyspnea | 2 | 1.1
Pharyngitis | 2 | 1.1
Skin and Appendages
Rash | 3 | 1.7
Urinary System Disorders
Dysuria | 8 | 4.6
Urinary retention | 2 | 1.1
Vision Disorders
Eye pain | 2 | 1.1
Conjunctivitis | 2 | 1.1

* Adverse reactions for TRELSTAR 11.25 mg are coded using the WHO Adverse Reactions Terminology (WHOART)

The following adverse reactions occurred in at least 5% of patients receiving TRELSTAR 22.5 mg. The table includes all reactions whether or not they were ascribed to TRELSTAR by the treating physician. The table also includes the incidence of these adverse reactions that were considered by the treating physician to have a reasonable causal relationship or for which the relationship could not be assessed.

Table 4. TRELSTAR 22.5 mg: Adverse Reactions Reported by 5% or More of Patients During Treatment
Adverse Reactions* | TRELSTAR 22.5 mg N = 120
Adverse Reactions* | Treatment-Emergent |  | Treatment-Related
Adverse Reactions* | N | % | N | %
General Disorders and Administration Site Conditions
Edema peripheral | 6 | 5.0 | 0 | 0
Infections and Infestations
Influenza | 19 | 15.8 | 0 | 0
Bronchitis | 6 | 5.0 | 0 | 0
Endocrine
Diabetes Mellitus/Hyperglycemia | 6 | 5.0 | 0 | 0
Musculoskeletal and Connective Tissue Disorders
Back pain | 13 | 10.8 | 1 | 0.8
Arthralgia | 9 | 7.5 | 1 | 0.8
Pain in extremity | 9 | 7.5 | 1 | 0.8
Nervous System Disorders
Headache | 9 | 7.5 | 2 | 1.7
Psychiatric Disorders
Insomnia | 6 | 5.0 | 1 | 0.8
Renal and Urinary Disorders
Urinary tract infection | 14 | 11.6 | 0 | 0
Urinary retention | 6 | 5.0 | 0 | 0
Reproductive System and Breast Disorders
Erectile dysfunction | 12 | 10.0 | 12 | 10.0
Testicular atrophy | 9 | 7.5 | 9 | 7.5
Vascular Disorders
Hot flush | 87 | 72.5 | 86 | 71.7
Hypertension | 17 | 14.2 | 1 | 0.8

* Adverse reactions for TRELSTAR 22.5 mg are coded using the Medical Dictionary for Regulatory Activities (MedDRA)

Changes in Laboratory Values During Treatment

The following abnormalities in laboratory values not present at baseline were observed in 10% or more of patients:

TRELSTAR 3.75 mg: There were no clinically meaningful changes in laboratory values detected during therapy.

TRELSTAR 11.25 mg: Decreased hemoglobin and RBC count and increased glucose, BUN, SGOT, SGPT, and alkaline phosphatase at the Day 253 visit.

TRELSTAR 22.5 mg: Decreased hemoglobin and increased glucose and hepatic transaminases were detected during the study. The majority of the changes were mild to moderate.

6.2 Post-marketing Experience

The following adverse reactions have been identified during post approval use of gonadotropin releasing hormone agonists. Because these reactions are reported voluntarily from a population of uncertain size, it is not always possible to reliably estimate their frequency or establish a causal relationship to drug exposure.

Pituitary Apoplexy – During post-marketing surveillance, rare cases of pituitary apoplexy (a clinical syndrome secondary to infarction of the pituitary gland) have been reported after the administration of gonadotropin-releasing hormone agonists. In majority of these cases, a pituitary adenoma was diagnosed with a majority of pituitary apoplexy cases occurring within 2 weeks of the first dose, and some within the first hour. In these cases, pituitary apoplexy has presented as sudden headache, vomiting, visual changes, ophthalmoplegia, altered mental status, and sometimes cardiovascular collapse. Immediate medical attention has been required.

Cardiovascular System – cerebrovascular accident, myocardial infarction, pulmonary emboli, thromboembolic events (including deep venous thrombosis, transient ischemic attack, and thrombophlebitis)

Central/Peripheral Nervous System – convulsions

Hepatobiliary Disorder – non-alcoholic fatty liver disease

Respiratory, Thoracic, and Mediastinal Disorder – interstitial lung disease

Skin and Subcutaneous Tissue Disorders – SJS/TEN, DRESS, AGEP, dermatitis exfoliative, bullous dermatitis, and erythema multiforme.

7 DRUG INTERACTIONS

No drug-drug interaction studies involving TRELSTAR have been conducted.

Human pharmacokinetic data with triptorelin suggest that C-terminal fragments produced by tissue degradation are either degraded completely within tissues, are rapidly degraded further in plasma, or cleared by the kidneys. Therefore, hepatic microsomal enzymes are unlikely to be involved in triptorelin metabolism. However, in the absence of relevant data and as a precaution, hyperprolactinemic drugs should not be used concomitantly with TRELSTAR since hyperprolactinemia reduces the number of pituitary GnRH receptors.

8 USE IN SPECIFIC POPULATIONS

8.1 Pregnancy

Risk Summary

Based on findings in animal studies and mechanism of action, TRELSTAR can cause fetal harm when administered to a pregnant woman [see Clinical Pharmacology (12.1)]. Expected hormonal changes that occur with TRELSTAR treatment increase the risk for pregnancy loss. In animal developmental and reproductive toxicology studies, daily administration of triptorelin to pregnant rats during the period of organogenesis caused maternal toxicity and embryo-fetal toxicities, including loss of pregnancy, at doses as low as 0.2, 0.8, and 8 times the estimated human daily dose based on body surface area. Advise pregnant patients and females of reproductive potential of the potential risk to the fetus.

Data

Animal Data

Studies in pregnant rats administered triptorelin at doses of 2, 10, and 100 mcg/kg/day (approximately equivalent to 0.2, 0.8, and 8 times the estimated human daily dose based on body surface area) during the period of organogenesis demonstrated maternal toxicity and embryo-fetal toxicities. Embryo-fetal toxicities consisted of pre-implantation loss, increased resorption, and reduced mean number of viable fetuses at the high dose. Teratogenic effects were not observed in viable fetuses in rats or mice. Doses administered to mice were 2, 20, and 200 mcg/kg/day (approximately equivalent to 0.1, 0.7, and 7 times the estimated human daily dose based on body surface area).

8.2 Lactation

The safety and efficacy of TRELSTAR have not been established in females. There are no data on the presence of triptorelin in human milk, the effects of the drug on milk production, or the effects of the drug on the breastfed child. Because of the potential for serious adverse reactions in a breastfed child from TRELSTAR, a decision should be made to either discontinue breastfeeding, or discontinue the drug taking into account the importance of the drug to the mother.

8.3 Females and Males of Reproductive Potential

Infertility

Males

Based on mechanism of action, TRELSTAR may impair fertility in males of reproductive potential [see Clinical Pharmacology (12.1)].

8.4 Pediatric Use

The safety and effectiveness of TRELSTAR in pediatric patients have not been established.

8.5 Geriatric Use

Prostate cancer occurs primarily in an older population. Clinical studies with TRELSTAR have been conducted primarily in patients ≥ 65 years [see Clinical Pharmacology (12.3) and Clinical Studies (14)].

8.6 Renal Impairment

Subjects with renal impairment had higher exposure than young healthy males [see Clinical Pharmacology (12.3)].

8.7 Hepatic Impairment

Subjects with hepatic impairment had higher exposure than young healthy males [see Clinical Pharmacology (12.3)].

11 DESCRIPTION

TRELSTAR is a white to slightly yellow lyophilized cake. When reconstituted, TRELSTAR has a milky appearance. It contains a pamoate salt of triptorelin, a synthetic decapeptide agonist analog of gonadotropin releasing hormone (GnRH). The chemical name of triptorelin pamoate is 5-oxo-L-prolyl-L-histidyl-L-tryptophyl-L-seryl-L-tyrosyl-D-tryptophyl-L-leucyl-L-arginyl-L-prolylglycine amide (pamoate salt). The empirical formula is C64H82N18O13 · C23H16O6 and the molecular weight is 1699.9. The structural formula is:

Structural formula for TRELSTAR (triptorelin pamoate).

The TRELSTAR products are sterile, lyophilized biodegradable microgranule formulations supplied as single dose vials. Refer to Table 5 for the composition of each TRELSTAR product.

Table 5. TRELSTAR Composition
Ingredients | TRELSTAR 3.75 mg | TRELSTAR 11.25 mg | TRELSTAR 22.5 mg
triptorelin pamoate (base units) | 3.75 mg | 11.25 mg | 22.5 mg
poly-d,l-lactide-co-glycolide | 138 mg | 120 mg | 183 mg
mannitol, USP | 71 mg | 74 mg | 74 mg
carboxymethylcellulose sodium, USP | 25 mg | 26 mg | 26 mg
polysorbate 80, NF | 1.7 mg | 1.7 mg | 1.7 mg

When 2 mL sterile water is added to the vial containing TRELSTAR and mixed, a suspension is formed which is intended as an intramuscular injection. TRELSTAR is available in a vial plus a vial adapter, and a separate pre-filled syringe that contains sterile water for injection, USP, 2 mL.

12 CLINICAL PHARMACOLOGY

12.1 Mechanism of Action

Triptorelin is a synthetic decapeptide agonist analog of gonadotropin releasing hormone (GnRH). Comparative in vitro studies showed that triptorelin was 100-fold more active than native GnRH in stimulating luteinizing hormone release from monolayers of dispersed rat pituitary cells in culture and 20-fold more active than native GnRH in displacing ^125I-GnRH from pituitary receptor sites. In animal studies, triptorelin pamoate was found to have 13‑fold higher luteinizing hormone-releasing activity and 21-fold higher follicle-stimulating hormone-releasing activity compared to the native GnRH.

12.2 Pharmacodynamics

Following the first administration, there is a transient surge in circulating levels of luteinizing hormone (LH), follicle-stimulating hormone (FSH), testosterone, and estradiol [see Adverse Reactions (6)]. After chronic and continuous administration, usually 2 to 4 weeks after initiation of therapy, a sustained decrease in LH and FSH secretion and marked reduction of testicular steroidogenesis are observed. A reduction of serum testosterone concentration to a level typically seen in surgically castrated men is obtained. Consequently, the result is that tissues and functions that depend on these hormones for maintenance become quiescent. These effects are usually reversible after cessation of therapy.

Following a single intramuscular injection of TRELSTAR:

TRELSTAR 3.75 mg: serum testosterone levels first increased, peaking on Day 4, and declined thereafter to low levels by Week 4 in healthy male volunteers.

TRELSTAR 11.25 mg: serum testosterone levels first increased, peaking on Days 2 – 3, and declined thereafter to low levels by Weeks 3 – 4 in men with advanced prostate cancer.

TRELSTAR 22.5 mg: serum testosterone levels first increased, peaking on Day 3, and declined thereafter to low levels by Weeks 3 – 4 in men with advanced prostate cancer.

12.3 Pharmacokinetics

Results of pharmacokinetic investigations conducted in healthy men indicate that after intravenous bolus administration, triptorelin is distributed and eliminated according to a 3-compartment model and corresponding half-lives are approximately 6 minutes, 45 minutes, and 3 hours.

Absorption

Following a single intramuscular injection of TRELSTAR to patients with prostate cancer, mean peak serum concentrations of 28.4 ng/mL, 38.5 ng/mL, and 44.1 ng/mL occurred in 1 to 3 hours after the 3.75 mg, 11.25 mg, and 22.5 mg formulations, respectively.

Triptorelin did not accumulate over 9 months (3.75 mg and 11.25 mg) or 12 months (22.5 mg) of treatment.

Distribution

The volume of distribution following a single intravenous bolus dose of 0.5 mg of triptorelin peptide was 30 – 33 L in healthy male volunteers. There is no evidence that triptorelin, at clinically relevant concentrations, binds to plasma proteins.

Elimination

Metabolism

The metabolism of triptorelin in humans is unknown but is unlikely to involve hepatic microsomal enzymes (cytochrome P-450). The effect of triptorelin on the activity of other drug metabolizing enzymes is also unknown. Thus far, no metabolites of triptorelin have been identified. Pharmacokinetic data suggest that C-terminal fragments produced by tissue degradation are either completely degraded in the tissues, or rapidly degraded in plasma, or cleared by the kidneys.

Excretion

Triptorelin is eliminated by both the liver and the kidneys. Following intravenous administration of 0.5 mg triptorelin peptide to six healthy male volunteers with a creatinine clearance of 149.9 mL/min, 41.7% of the dose was excreted in urine as intact peptide with a total triptorelin clearance of 211.9 mL/min. This percentage increased to 62.3% in patients with liver disease who have a lower creatinine clearance (89.9 mL/min). It has also been observed that the nonrenal clearance of triptorelin (patient anuric, CIcreat = 0) was 76.2 mL/min, thus indicating that the nonrenal elimination of triptorelin is mainly dependent on the liver.

Specific Populations

Age and Race

The effects of age and race on triptorelin pharmacokinetics have not been systematically studied. However, pharmacokinetic data obtained in young healthy male volunteers aged 20 to 22 years with an elevated creatinine clearance (approximately 150 mL/min) indicate that triptorelin was eliminated twice as fast in this young population as compared with patients with moderate renal insufficiency. This is related to the fact that triptorelin clearance is partly correlated to total creatinine clearance, which is well known to decrease with age [see Use in Specific Populations (8.6) and (8.7)].

Pediatric

TRELSTAR has not been evaluated in patients less than 18 years of age [see Use in Specific Populations (8.4)].

Hepatic and Renal Impairment

After an intravenous bolus injection of 0.5 mg triptorelin, the two distribution half-lives were unaffected by renal and hepatic impairment. However, renal insufficiency led to a decrease in total triptorelin clearance proportional to the decrease in creatinine clearance as well as increases in volume of distribution and consequently, an increase in elimination half-life (see Table 6). In subjects with hepatic insufficiency, a decrease in triptorelin clearance was more pronounced than that observed with renal insufficiency. Due to minimal increases in the volume of distribution, the elimination half-life in subjects with hepatic insufficiency was similar to subjects with renal insufficiency. Subjects with renal or hepatic impairment had 2‑ to 4-fold higher exposure (AUC values) than young healthy males [see Use in Specific Populations (8.6) and (8.7)].

Table 6. Pharmacokinetic Parameters (Mean ± SD) in Healthy Volunteers and Special Populations Following an IV Bolus Injection of 0.5 mg Triptorelin
Group | Cmax (ng/mL) | AUCinf (h·ng/mL) | Clp (mL/min) | Clrenal (mL/min) | t 1/2 (h) | Clcreat (mL/min)
6 healthy male volunteers | 48.2 ±11.8 | 36.1 ±5.8 | 211.9 ±31.6 | 90.6 ±35.3 | 2.81 ±1.21 | 149.9 ±7.3
6 males with moderate renal impairment | 45.6 ±20.5 | 69.9 ±24.6 | 120.0 ±45.0 | 23.3 ±17.6 | 6.56 ±1.25 | 39.7 ±22.5
6 males with severe renal impairment | 46.5 ±14.0 | 88.0 ±18.4 | 88.6 ±19.7 | 4.3 ±2.9 | 7.65 ±1.25 | 8.9 ±6.0
6 males with liver disease | 54.1 ±5.3 | 131.9 ±18.1 | 57.8 ±8.0 | 35.9 ±5.0 | 7.58 ±1.17 | 89.9 ±15.1

13 NONCLINICAL TOXICOLOGY

13.1 Carcinogenesis, Mutagenesis, Impairment of Fertility

In rats, triptorelin doses of 120, 600, and 3000 mcg/kg given every 28 days (approximately 0.3, 2, and 8 times the human monthly dose based on body surface area) resulted in increased mortality with a drug treatment period of 13 – 19 months. The incidences of benign and malignant pituitary tumors and histiosarcomas were increased in a dose-related manner. No oncogenic effect was observed in mice administered triptorelin for 18 months at doses up to 6000 mcg/kg every 28 days (approximately 8 times the human monthly dose based on body surface area).

Mutagenicity studies performed with triptorelin using bacterial and mammalian systems (in vitro Ames test and chromosomal aberration test in CHO cells and an in vivo mouse micronucleus test) provided no evidence of mutagenic potential.

After 60 days of subcutaneous treatment followed by a minimum of four estrus cycles prior to mating, triptorelin, at doses of 2, 20, and 200 mcg/kg/day in saline (approximately 0.2, 2, and 16 times the estimated human daily dose based on body surface area) or 2 monthly injections as slow release microspheres (~20 mcg/kg/day), had no effect on the fertility or general reproductive function of female rats.

No studies were conducted to assess the effect of triptorelin on male fertility.

14 CLINICAL STUDIES

TRELSTAR 3.75 mg

TRELSTAR 3.75 mg was studied in a randomized, active control trial of 277 men with advanced prostate cancer. The clinical trial population consisted of 59.9% Caucasian, 39.3% Black, and 0.8% Other. There was no difference observed with triptorelin response between racial groups. Men were between 47 and 89 years of age (mean = 71 years). Patients received either TRELSTAR 3.75 mg (N = 140) or an approved GnRH agonist monthly for 9 months. The primary efficacy endpoints were both achievement of castration by Day 29 and maintenance of castration from Day 57 through Day 253.

Castration levels of serum testosterone (≤ 1.735 nmol/L; equivalent to 50 ng/dL) in patients treated with TRELSTAR 3.75 mg were achieved at Day 29 in 125 of 137 (91.2%) patients and at Day 57 in 97.7% of patients. Maintenance of castration levels of serum testosterone from Day 57 through Day 253 was found in 96.2% of patients treated with TRELSTAR 3.75 mg.

The presence of an acute-on-chronic flare phenomenon was also studied as a secondary efficacy endpoint. Serum LH levels were measured at 2 hours after repeat TRELSTAR 3.75 mg administration on Days 85 and 169. One hundred twenty-four of the 126 evaluable patients (98.4%) on Day 85 had a serum LH level of ≤ 1.0 IU/L at 2 hours after dosing, indicating desensitization of the pituitary gonadotroph receptors.

TRELSTAR 11.25 mg

TRELSTAR 11.25 mg was studied in a randomized, active control trial of 346 men with advanced prostate cancer. The clinical trial population consisted of 48% Caucasian, 38% Black, and 15% Other. There was no difference observed with triptorelin response between racial groups. Men were between 45 and 96 years of age (mean = 71 years). Patients received either TRELSTAR 11.25 mg (N = 174) every 12 weeks for a total of up to 3 doses (maximum treatment period of 253 days) or TRELSTAR 3.75 mg (N = 172) every 28 days for a total of up to 9 doses. The primary efficacy endpoints were both achievement of castration by Day 29 and maintenance of castration from Day 57 through Day 253.

Castration levels of serum testosterone (≤ 1.735 nmol/L; equivalent to 50 ng/dL) were achieved at Day 29 in 167 of 171 (97.7%) patients treated with TRELSTAR 11.25 mg, and maintenance of castration levels of serum testosterone from Day 57 through Day 253 was found in 94.4% of patients treated with TRELSTAR 11.25 mg.

TRELSTAR 22.5 mg

TRELSTAR 22.5 mg was studied in a non-comparative trial of 120 men with advanced prostate cancer. The clinical trial population consisted of 64% Caucasian, 23% Black, and 13% Other, with a mean age of 71.1 years (range 51-93). Patients received TRELSTAR 22.5 mg (N = 120) every 24 weeks for a total of 2 doses (maximum treatment period of 337 days). The primary efficacy endpoints included achievement of castration by Day 29 and maintenance of castration from Day 57 through Day 337.

Castration levels of serum testosterone (≤ 1.735 nmol/L; equivalent to 50 ng/dL) were achieved at Day 29 in 97.5% (117 of 120) of patients treated with TRELSTAR 22.5 mg. Castration was maintained in 93.3% of patients in the period from Day 57 to Day 337.

A summary of the clinical studies for TRELSTAR is provided in Table 7.

Table 7. Summary of TRELSTAR Clinical Studies
Product Strength | 3.75 mg | 11.25 mg | 22.5 mg
Number of Patients | 137 | 171 | 120
Treatment Schedule | every 4 weeks | every 12 weeks | every 24 weeks
Duration of Study | 253 days | 253 days | 337 days
Castration Rate* on Day 29, % (n/N) | 91.2% (125/137) | 97.7% (167/171) | 97.5% (117/120)
Rate of Castration Maintenance† from Days 57 – 253, % | 96.2% | 94.4% | not applicable
Rate of Castration Maintenance from Days 57 – 337, % (n/N) | not applicable | not applicable | 93.3% (112/120)‡

* Maintenance of castration was calculated using a frequency distribution.
† Cumulative maintenance of castration was calculated using a survival analysis (Kaplan-Meier) technique.
‡ Calculation includes 5 patients who discontinued the study but who had castrate levels of testosterone prior to discontinuation.

16 HOW SUPPLIED/STORAGE AND HANDLING

TRELSTAR (triptorelin pamoate for injectable suspension) is supplied as a single dose vial with a Flip-Off cap containing sterile lyophilized triptorelin pamoate microgranules incorporated in a biodegradable copolymer of lactic and glycolic acids, with injection kit consisting of a vial adapter, a 21 gauge 1 ½” injection needle, and a pre-filled syringe containing sterile water for injection, USP, 2 mL.

TRELSTAR 3.75 mg – NDC 74676-5902-1: 3.75 mg of slightly yellow microgranules provided in a vial with a violet flip-off cap with injection kit.

TRELSTAR 11.25 mg – NDC 74676-5904-1: 11.25 mg of slightly yellow microgranules provided in a vial with a yellow green flip-off cap with injection kit.

TRELSTAR 22.5 mg – NDC 74676-5906-1: 22.5 mg of slightly yellow microgranules provided in a vial with a dark green flip-off cap with injection kit.

Storage

Store at 20-25°C (68-77°F). [See USP Controlled Room Temperature.] Do not freeze TRELSTAR.

17 PATIENT COUNSELING INFORMATION

Hypersensitivity

- Inform patients that if they have experienced hypersensitivity with other GnRH agonist drugs like TRELSTAR, TRELSTAR is contraindicated [see Contraindications (4)].

Tumor Flare

- Inform patients that TRELSTAR can cause tumor flare during the first weeks of treatment. Inform patients that the increase in testosterone can cause an increase in urinary symptoms or pain. Advise patients to contact their healthcare provider if urethral obstruction, spinal cord compression, paralysis, or new or worsened symptoms occur after beginning TRELSTAR treatment [see Warnings and Precautions (5.2) ].

Metabolic Syndrome

- Advise patients that there is an increased risk of metabolic changes such as hyperglycemia, diabetes, hyperlipidemia, and non-alcoholic fatty liver disease with TRELSTAR therapy. Inform patients that periodic monitoring for hyperglycemia and diabetes is required when being treated with TRELSTAR [see Warnings and Precautions (5.3)].

Cardiovascular Disease

- Inform patients that there is an increased risk of myocardial infarction, sudden cardiac death, and stroke with TRELSTAR treatment. Advise patients to immediately report signs and symptoms associated with these events to their healthcare provider for evaluation [see Warnings and Precautions (5.4) ].

Convulsions

- Inform patients that there is an increased risk of convulsions with TRELSTAR treatment. Advise patients to immediately contact their healthcare provider if they experience convulsions [see Warnings and Precautions (5.5)].

Severe Cutaneous Adverse Reactions

- Inform patients that severe cutaneous adverse reactions (SCARs), including Stevens-Johnson syndrome (SJS), toxic epidermal necrolysis (TEN), drug reaction with eosinophilia and systemic symptoms (DRESS), and acute generalized exanthematous pustulosis (AGEP), which may be life threatening or fatal, may occur during treatment with TRELSTAR.
  Advise patients to contact their healthcare provider or seek medical attention right away if they experience signs or symptoms of SCARs, e.g. a prodrome of fever, flu-like symptoms, mucosal lesions, progressive skin rash, or lymphadenopathy [see Warnings and Precautions (5.6)].

Urogenital Disorders

- Advise patients that TRELSTAR may cause impotence.

Infertility

- Inform patients that TRELSTAR may cause infertility [(see Use In Specific Populations (8.3)].

Continuation of TRELSTAR Treatment

- Inform patients that TRELSTAR is usually continued, often with additional medication, after the development of metastatic castration-resistant prostate cancer [see Dosage and Administration (2.1)].

For all medical inquiries contact:
Verity Pharma, Medical Affairs
1-844-VERITY-1 (1-844-837-4891)

Distributed by:
Verity Pharmaceuticals, Inc.
Ewing, NJ 08628

Manufactured by:
Debiopharm Research & Manufacturing SA
CH-1920 Martigny, Switzerland

TRELSTAR® and its design are registered trademarks of Verity Pharmaceuticals, Inc.

Verity Pharmaceuticals, Verity Pharma, and their designs are trademarks of Verity Pharmaceuticals, Inc.

© 2025 Verity Pharmaceuticals Inc. All rights reserved.

PACKAGE LABEL

PRINCIPAL DISPLAY PANEL
Trelstar 3.75 mg
3.75 mg every 4 weeks

PACKAGE LABEL

Trelstar 3.75 mg Vial

PACKAGE LABEL

PRINCIPAL DISPLAY PANEL
Trelstar 11.25 mg
11.25 mg every 12 weeks

PACKAGE LABEL

Trelstar 11.25 mg Vial

PACKAGE LABEL

PRINCIPAL DISPLAY PANEL
Trelstar 22.5 mg
22.5 mg every 24 weeks

PACKAGE LABEL

Trelstar 22.5 mg Vial